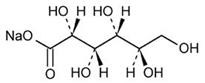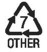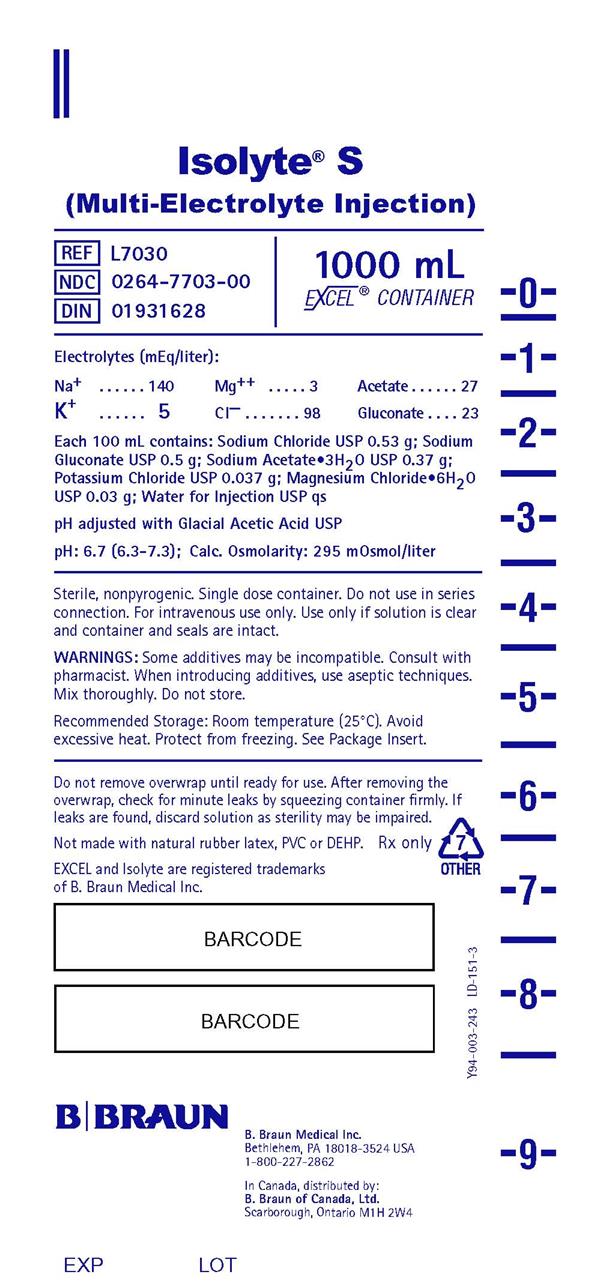 DRUG LABEL: Isolyte S
NDC: 0264-7703 | Form: INJECTION, SOLUTION
Manufacturer: B. Braun Medical Inc.
Category: prescription | Type: HUMAN PRESCRIPTION DRUG LABEL
Date: 20200514

ACTIVE INGREDIENTS: SODIUM CHLORIDE 0.53 g/100 mL; SODIUM GLUCONATE 0.5 g/100 mL; SODIUM ACETATE 0.37 g/100 mL; POTASSIUM CHLORIDE 0.037 g/100 mL; MAGNESIUM CHLORIDE 0.03 g/100 mL
INACTIVE INGREDIENTS: WATER

Isolyte® S
(Multi-Electrolyte Injection)

DESCRIPTION

Each 100 mL of Isolyte® S (Multi-Electrolyte Injection) contains:
Sodium Chloride USP 0.53 g; Sodium Gluconate USP 0.5 g
Sodium Acetate Trihydrate USP 0.37 g; Potassium Chloride USP 0.037 g
Magnesium Chloride Hexahydrate USP 0.03 g
Water for Injection USP qs

pH adjusted with Glacial Acetic Acid USP
pH: 6.7 (6.3–7.3)
Calculated Osmolarity: 295 mOsmol/liter

Concentration of Electrolytes (mEq/liter): Sodium 140; Potassium 5
Magnesium 3; Chloride 98; Acetate (CH3COO^−) 27
Gluconate (HOCH2(CHOH)4COO^−) 23

Isolyte® S is sterile, nonpyrogenic, and contains no bacteriostatic or antimicrobial agents.

The formulas of the active ingredients are:

Ingredients | Molecular Formula | Molecular Weight
Sodium Chloride USP | NaCl | 58.44
Sodium Acetate Trihydrate USP | CH3COONa•3H2O | 136.08
Potassium Chloride USP | KCl | 74.55
Magnesium Chloride Hexahydrate USP | MgCl2•6H2O | 203.30
Sodium Gluconate USP |  | 218.14

Not made with natural rubber latex, PVC or DEHP.

The plastic container is made from a multilayered film specifically developed for parenteral drugs. It contains no plasticizers and exhibits virtually no leachables. The solution contact layer is a rubberized copolymer of ethylene and propylene. The container is nontoxic and biologically inert. The container-solution unit is a closed system and is not dependent upon entry of external air during administration. The container is overwrapped to provide protection from the physical environment and to provide an additional moisture barrier when necessary.

Addition of medication should be accomplished using complete aseptic technique.

The closure system has two ports; the one for the administration set has a tamper evident plastic protector and the other is a medication addition site. Refer to the Directions for Use of the container.

CLINICAL PHARMACOLOGY

Isolyte® S provides electrolytes and is a source of water for hydration. It is capable of inducing diuresis depending on the clinical condition of the patient.

Sodium, the major cation of the extracellular fluid, functions primarily in the control of water distribution, fluid balance, and osmotic pressure of body fluids. Sodium is also associated with chloride and bicarbonate in the regulation of the acid-base equilibrium of body fluid.

Potassium, the principal cation of intracellular fluid, participates in carbohydrate utilization and protein synthesis, and is critical in the regulation of nerve conduction and muscle contraction, particularly in the heart.

Chloride, the major extracellular anion, closely follows the metabolism of sodium, and changes in the acid-base balance of the body are reflected by changes in the chloride concentration.

Magnesium, a principal cation of soft tissue, is primarily involved in enzyme activity associated with the metabolism of carbohydrates and protein. Magnesium is also involved in neuromuscular irritability.

Gluconate and acetate are organic ions which are hydrogen ion acceptors and contribute bicarbonate during their metabolism to carbon dioxide and water.

INDICATIONS AND USAGE

This solution is indicated for use in adults and pediatric patients as a source of electrolytes and water for hydration, and as an alkalinizing agent.

CONTRAINDICATIONS

This solution is contraindicated where the administration of sodium, potassium, magnesium, chloride, acetate or gluconate could be clinically detrimental.

WARNINGS

The administration of intravenous solutions can cause fluid and/or solute overload resulting in dilution of serum electrolyte concentrations, overhydration, congested states or pulmonary edema. The risk of dilutional states is inversely proportional to the electrolyte concentration. The risk of solute overload causing congested states with peripheral and pulmonary edema is directly proportional to the electrolyte concentration.

Solutions containing sodium ions should be used with great care, if at all, in patients with congestive heart failure, severe renal insufficiency, and in clinical states in which there is sodium retention with edema.

Solutions containing potassium ions should be used with great care, if at all, in patients with hyperkalemia, severe renal failure, and in conditions in which potassium retention is present.

In patients with diminished renal function, administration of solutions containing sodium or potassium ions may result in sodium or potassium retention.

Solutions containing gluconate or acetate should be used with great care in patients with metabolic or respiratory alkalosis and in those conditions in which there is an increased level or an impaired utilization of these ions, such as severe hepatic insufficiency.

PRECAUTIONS

General

Clinical evaluation and periodic laboratory determinations are necessary to monitor changes in fluid balance, electrolyte concentrations, and acid-base balance during prolonged parenteral therapy or whenever the condition of the patient warrants such evaluation. Significant deviations from normal concentrations may require tailoring of the electrolyte pattern, in this or an alternative solution.

This solution should be used with care in patients with hypervolemia, renal insufficiency, urinary tract obstruction, or impending or frank cardiac decompensation.

Extraordinary electrolyte losses such as may occur during protracted nasogastric suction, vomiting, diarrhea or gastrointestinal fistula drainage may necessitate additional electrolyte supplementation.

Additional essential electrolytes, minerals, and vitamins should be supplied as needed.

Sodium-containing solutions should be administered with caution to patients receiving corticosteroids or corticotropin, or to other salt-retaining patients.

Potassium therapy should be guided primarily by serial electrocardiograms, especially in patients receiving digitalis. Serum potassium levels are not necessarily indicative of tissue potassium levels.

Care should be exercised in administering solutions containing sodium or potassium to patients with renal or cardiovascular insufficiency, with or without congestive heart failure, particularly if they are postoperative or elderly.

Solutions containing potassium or magnesium should be used with caution in the presence of cardiac disease, particularly when accompanied by renal disease.

Parenteral magnesium should be administered with extreme caution to patients receiving digitalis preparations.

Administration of barbiturates, narcotics, hypnotics or systemic anesthetics should be adjusted with caution in patients also receiving magnesium-containing solutions because of an additive central depressive effect.

Solutions containing gluconate or acetate should be used with caution. Excess administration may result in metabolic alkalosis.

To minimize the risk of possible incompatibilities arising from mixing this solution with other additives that may be prescribed, the final infusate should be inspected for cloudiness or precipitation immediately after mixing, prior to administration, and periodically during administration.

Do not use plastic containers in series connection.

If administration is controlled by a pumping device, care must be taken to discontinue pumping action before the container runs dry or air embolism may result. If administration is not controlled by a pumping device, refrain from applying excessive pressure (>300mmHg) causing distortion to the container such as wringing or twisting. Such handling could result in breakage of the container.

This solution is intended for intravenous administration using sterile equipment. It is recommended that intravenous administration apparatus be replaced at least once every 24 hours.

Use only if solution is clear and container and seals are intact.

Pregnancy

Teratogenic Effects

Animal reproduction studies have not been conducted with Isolyte® S (Multi-Electrolyte Injection). It is also not known whether Isolyte S can cause fetal harm when administered to a pregnant woman or can affect reproduction capacity. Isolyte S should be given to a pregnant woman only if clearly needed.

Pediatric Use

Safety and effectiveness of Isolyte® S (Multi-Electrolyte Injection) in pediatric patients have not been established by adequate and well controlled trials. However, the use of multi-electrolyte solutions in the pediatric population is referenced in the medical literature. The warnings, precautions, and adverse reactions identified in the label copy should be observed in the pediatric population.

Geriatric Use

Clinical studies of Isolyte® S (Multi-Electrolyte Injection) did not include sufficient numbers of subjects aged 65 and over to determine whether they respond differently from younger subjects. Other reported clinical experience has not identified differences in responses between the elderly and younger patients. In general, dose selection for an elderly patient should be cautious, usually starting at the low end of the dosing range, reflecting the greater frequency of decreased hepatic, renal, or cardiac function, and of concomitant disease or other drug therapy.

ADVERSE REACTIONS

Reactions which may occur because of the solution or the technique of administration include febrile response, infection at the site of injection, venous thrombosis or phlebitis extending from the site of injection, extravasation and hypervolemia.

Symptoms may result from an excess or deficit of one or more of the ions present in the solution; therefore, frequent monitoring of electrolyte levels is essential.

Hypernatremia may be associated with edema and exacerbation of congestive heart failure due to the retention of water, resulting in an expanded extracellular fluid volume.

Reactions reported with the use of potassium-containing solutions include nausea, vomiting, abdominal pain and diarrhea. The signs and symptoms of potassium intoxication include paresthesias of the extremities, areflexia, muscular or respiratory paralysis, mental confusion, weakness, hypotension, cardiac arrhythmias, heart block, electrocardiographic abnormalities and cardiac arrest. Potassium deficits result in disruption of neuromuscular function, and intestinal ileus and dilatation.

If infused in large amounts, chloride ions may cause a loss of bicarbonate ions, resulting in an acidifying effect.

Abnormally high plasma levels of magnesium can result in flushing, sweating, hypotension, circulatory collapse, and depression of cardiac and central nervous system function. Respiratory depression is the most immediate threat to life. Magnesium deficits can result in tachycardia, hypertension, hyperirritability and psychotic behavior.

The physician should also be alert to the possibility of adverse reactions to drug additives. Prescribing information for drug additives to be administered in this manner should be consulted.

If an adverse reaction does occur, discontinue the infusion, evaluate the patient, institute appropriate therapeutic countermeasures and save the remainder of the fluid for examination if deemed necessary.

OVERDOSAGE

In the event of a fluid or solute overload during parenteral therapy, reevaluate the patient's condition, and institute appropriate corrective treatment.

In the event of overdosage with potassium-containing solutions, discontinue the infusion immediately and institute corrective therapy to reduce serum potassium levels.

Treatment of hyperkalemia includes the following:

1. Dextrose Injection USP, 10% or 25%, containing 10 units of crystalline insulin per 20 grams of dextrose administered intravenously, 300 to 500 mL per hour.
2. Absorption and exchange of potassium using sodium or ammonium cycle cation exchange resin, orally and as retention enema.
3. Hemodialysis and peritoneal dialysis. The use of potassium-containing foods or medications must be eliminated. However, in cases of digitalization, too rapid a lowering of plasma potassium concentration can cause digitalis toxicity.

DOSAGE AND ADMINISTRATION

This solution is for intravenous use only.

Dosage is to be directed by a physician and is dependent upon age, weight, clinical condition of the patient and laboratory determinations. Frequent laboratory determinations and clinical evaluation are essential to monitor changes in blood glucose and electrolyte concentrations, and fluid and electrolyte balance during prolonged parenteral therapy.

Fluid administration should be based on calculated maintenance or replacement fluid requirements for each patient.

Isolyte® S (Multi-Electrolyte Injection) contains no phosphate. It may be admixed with solutions which contain phosphate or which have been supplemented with phosphate. The presence of calcium and magnesium ions should be considered when phosphate is present in the additive solution, in order to avoid precipitation.

Some additives may be incompatible. Consult with pharmacist. When introducing additives, use aseptic techniques. Mix thoroughly. Do not store.

Parenteral drug products should be inspected visually for particulate matter and discoloration prior to administration, whenever solution and container permit.

HOW SUPPLIED

Isolyte® S (Multi-Electrolyte Injection) is supplied sterile and nonpyrogenic in 1000 mL EXCEL® Containers packaged 12 per case.

NDC | REF | Size
Isolyte® S (Multi-Electrolyte Injection) (Canada DIN 01931628)
0264-7703-00 | L7030 | 1000 mL

STORAGE AND HANDLING

Exposure of pharmaceutical products to heat should be minimized. Avoid excessive heat. Protect from freezing. It is recommended that the product be stored at room temperature (25°C); however, brief exposure up to 40°C does not adversely affect the product.

Rx only

Revised: July 2018

EXCEL and Isolyte are registered trademarks of B. Braun Medical Inc.

Directions for Use of EXCEL® Container

Caution: Do not use plastic containers in series connection.

To Open

Tear overwrap down at notch and remove solution container. Check for minute leaks by squeezing solution container firmly. If leaks are found, discard solution as sterility may be impaired. If supplemental medication is desired, follow directions below before preparing for administration.

NOTE: Before use, perform the following checks:

- Inspect each container. Read the label. Ensure solution is the one ordered and is within the expiration date.
- Invert container and carefully inspect the solution in good light for cloudiness, haze, or particulate matter. Any container which is suspect should not be used.
- Use only if solution is clear and container and seals are intact.

Preparation for Administration

1. Remove plastic protector from sterile set port at bottom of container.
2. Attach administration set. Refer to complete directions accompanying set.

To Add Medication

Warning: Some additives may be incompatible.

To Add Medication Before Solution Administration

1. Prepare medication site.
2. Using syringe with 18–22 gauge needle, puncture medication port and inner diaphragm and inject.
3. Squeeze and tap ports while ports are upright and mix solution and medication thoroughly.

To Add Medication During Solution Administration

1. Close clamp on the set.
2. Prepare medication site.
3. Using syringe with 18–22 gauge needle of appropriate length (at least 5/8 inch), puncture resealable medication port and inner diaphragm and inject.
4. Remove container from IV pole and/or turn to an upright position.
5. Evacuate both ports by tapping and squeezing them while container is in the upright position.
6. Mix solution and medication thoroughly.
7. Return container to in use position and continue administration.

B. Braun Medical Inc.
Bethlehem, PA 18018-3524 USA
1-800-227-2862

In Canada, distributed by:
B. Braun of Canada, Ltd.
Scarborough, Ontario M1H 2W4

Y36-002-951 LD-500-2

PRINCIPAL DISPLAY PANEL - 1000 mL Container Label

Isolyte® S
(Multi-Electrolyte Injection)

REF L7030
NDC 0264-7703-00
DIN 01931628

1000 mL
EXCEL® CONTAINER

Electrolytes (mEq/liter):

Na^+ 140 Mg^++ 3 Acetate 27
K^+ 5 Cl^– 98 Gluconate 23

Each 100 mL contains: Sodium Chloride USP 0.53 g; Sodium
Gluconate USP 0.5 g; Sodium Acetate•3H2O USP 0.37 g;
Potassium Chloride USP 0.037 g; Magnesium Chloride•6H2O
USP 0.03 g; Water for Injection USP qs

pH adjusted with Glacial Acetic Acid USP

pH: 6.7 (6.3-7.3); Calc. Osmolarity: 295 mOsmol/liter

Sterile, nonpyrogenic. Single dose container. Do not use in series
connection. For intravenous use only. Use only if solution is clear
and container and seals are intact.

WARNINGS: Some additives may be incompatible. Consult with
pharmacist. When introducing additives, use aseptic techniques.
Mix thoroughly. Do not store.

Recommended Storage: Room temperature (25°C). Avoid
excessive heat. Protect from freezing. See Package Insert.

Do not remove overwrap until ready for use. After removing the
overwrap, check for minute leaks by squeezing container firmly. If
leaks are found, discard solution as sterility may be impaired.

Not made with natural rubber latex, PVC or DEHP.

Rx only

EXCEL and Isolyte are registered trademarks
of B. Braun Medical Inc.

B. Braun Medical Inc.
Bethlehem, PA 18018-3524 USA
1-800-227-2862

In Canada, distributed by:
B. Braun of Canada, Ltd.
Scarborough, Ontario M1H 2W4

Y94-003-243
LD-151-3

EXP

LOT